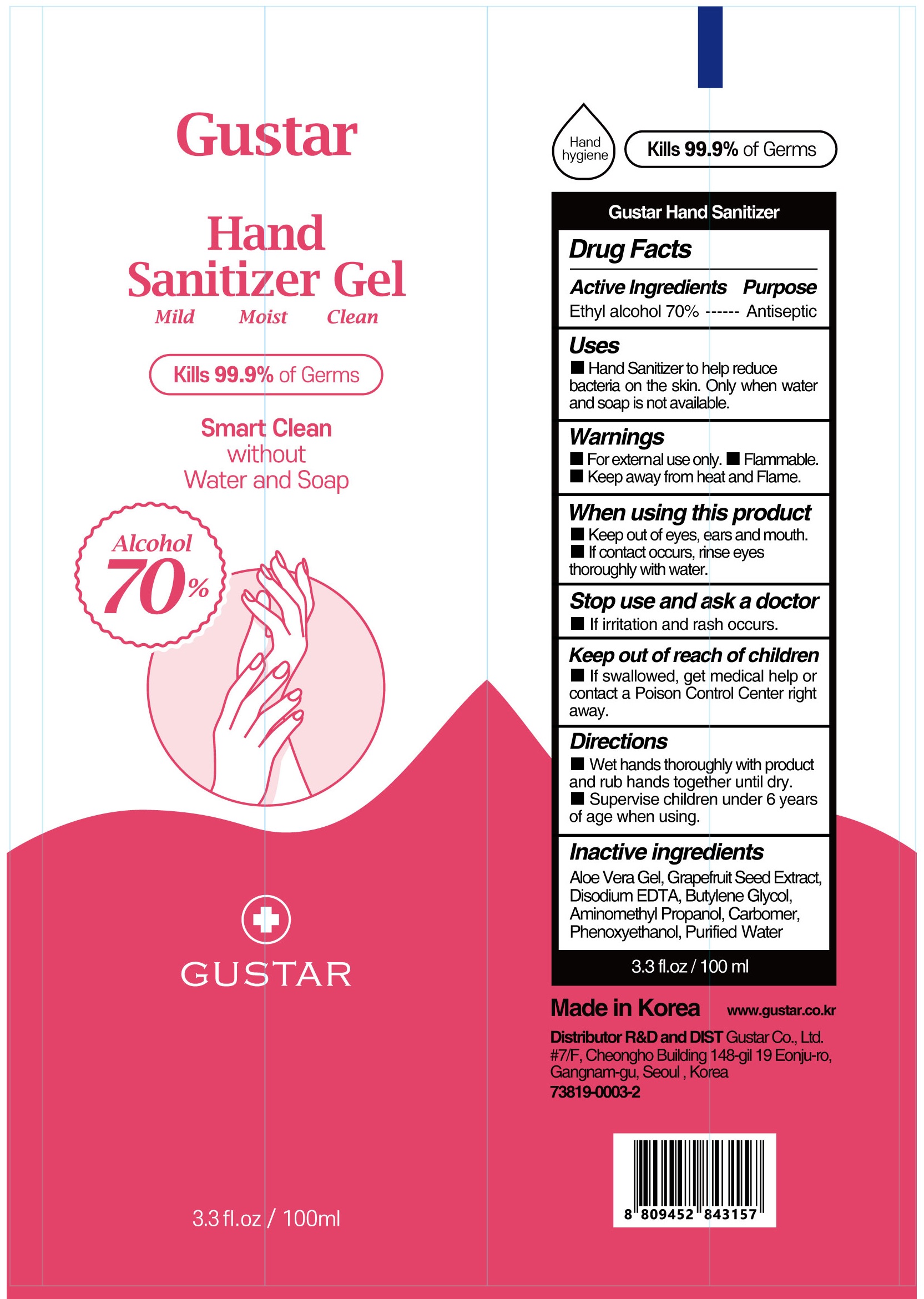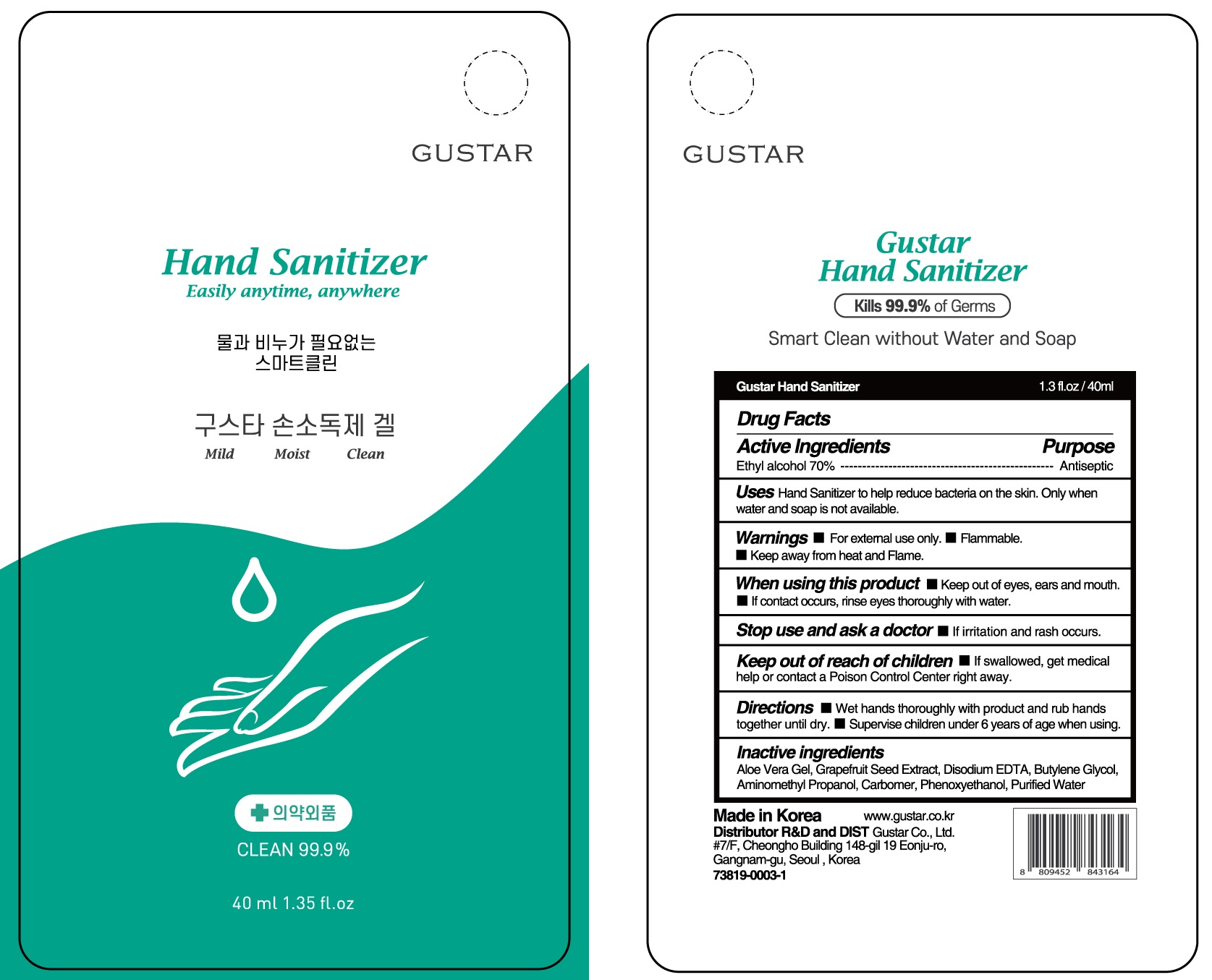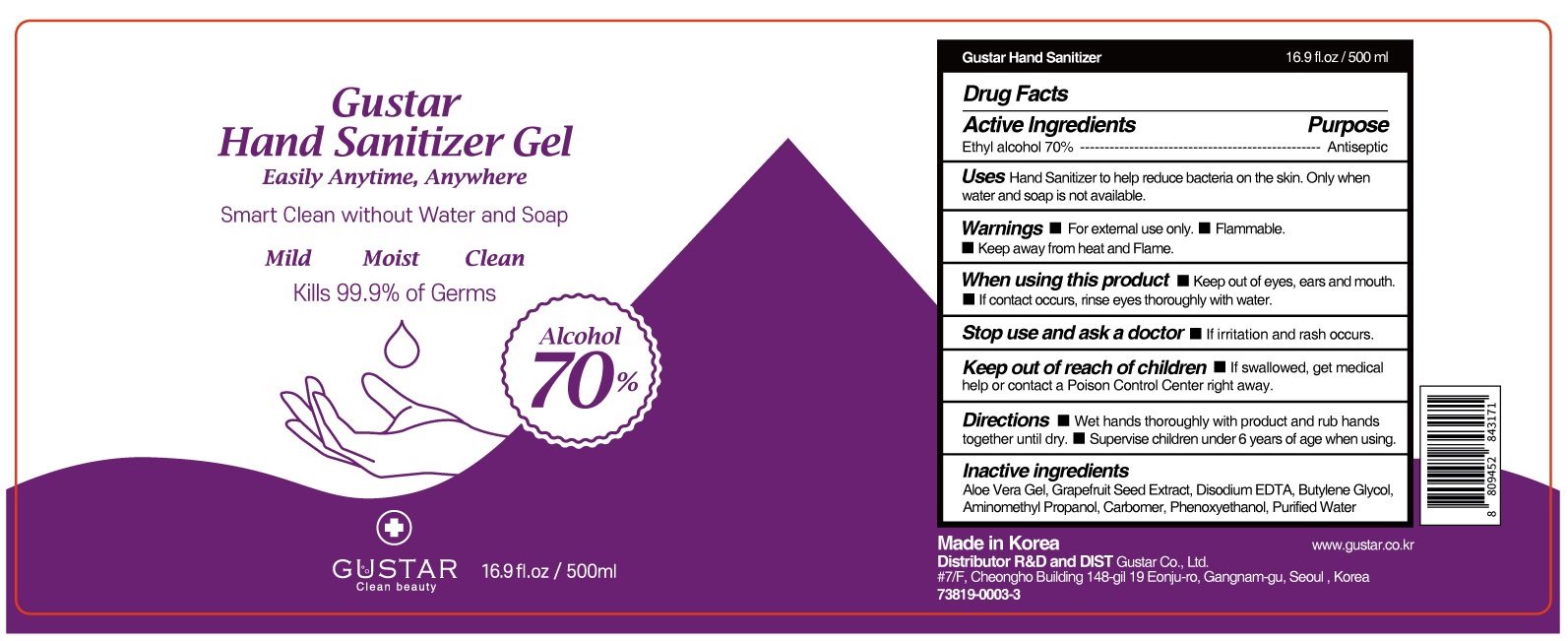 DRUG LABEL: GUSTAR HAND SANITIZER (ETHANOL)
NDC: 73819-0003 | Form: GEL
Manufacturer: GuStar Co Ltd
Category: otc | Type: HUMAN OTC DRUG LABEL
Date: 20200526

ACTIVE INGREDIENTS: ALCOHOL 70 g/100 mL
INACTIVE INGREDIENTS: BUTYLENE GLYCOL; ALOE VERA LEAF; WATER; GRAPEFRUIT SEED OIL

Drug Facts

ACTIVE INGREDIENT

Ethyl alcohol 70%

INACTIVE INGREDIENTS

Aloe Vera Gel, Grapefruit Seed Extract, Disodium EDTA, Butylene Glycol, Aminomethyl Propanol, Carbomer, Phenoxyethanol, Purified Water

PURPOSE

Antiseptic

WARNINGS

■ For external use only.
■ Flammable. ■ Keep away from heat and Flame.

When using this product
■ Keep out of eyes, ears and mouth.
■ If contact occurs, rinse eyes thoroughly with water

Stop use and ask a doctor
■ If irritation and rash occurs.

KEEP OUT OF REACH OF CHILDREN

■ lf swallowed, get medical help or contact a Poison Control Center right away.

Uses

Hand sanitizer to help reduce bacteria on the skin. Only when water and soap is not available.

Directions

■ Wet hands thoroughly with product and rub hands together until dry.
■ Supervise children under 6 years of age when using